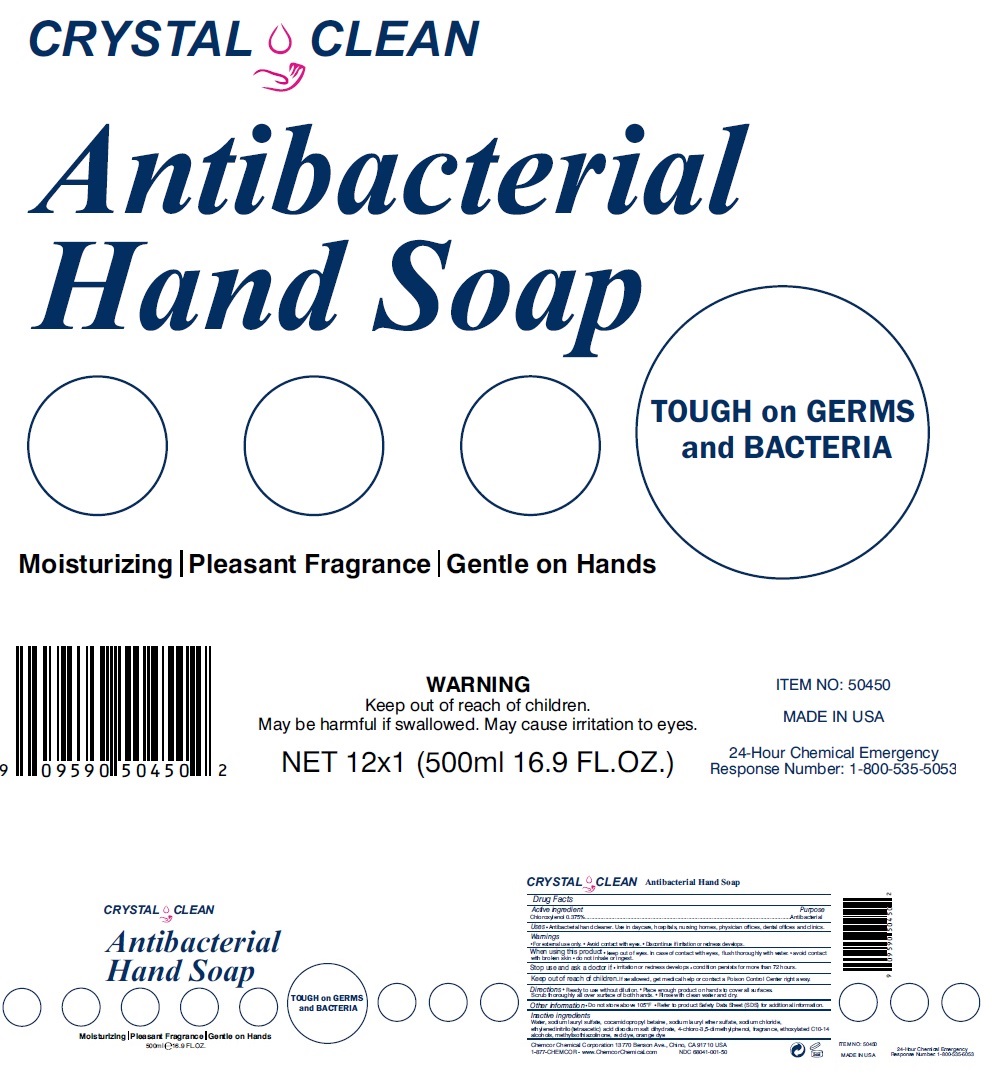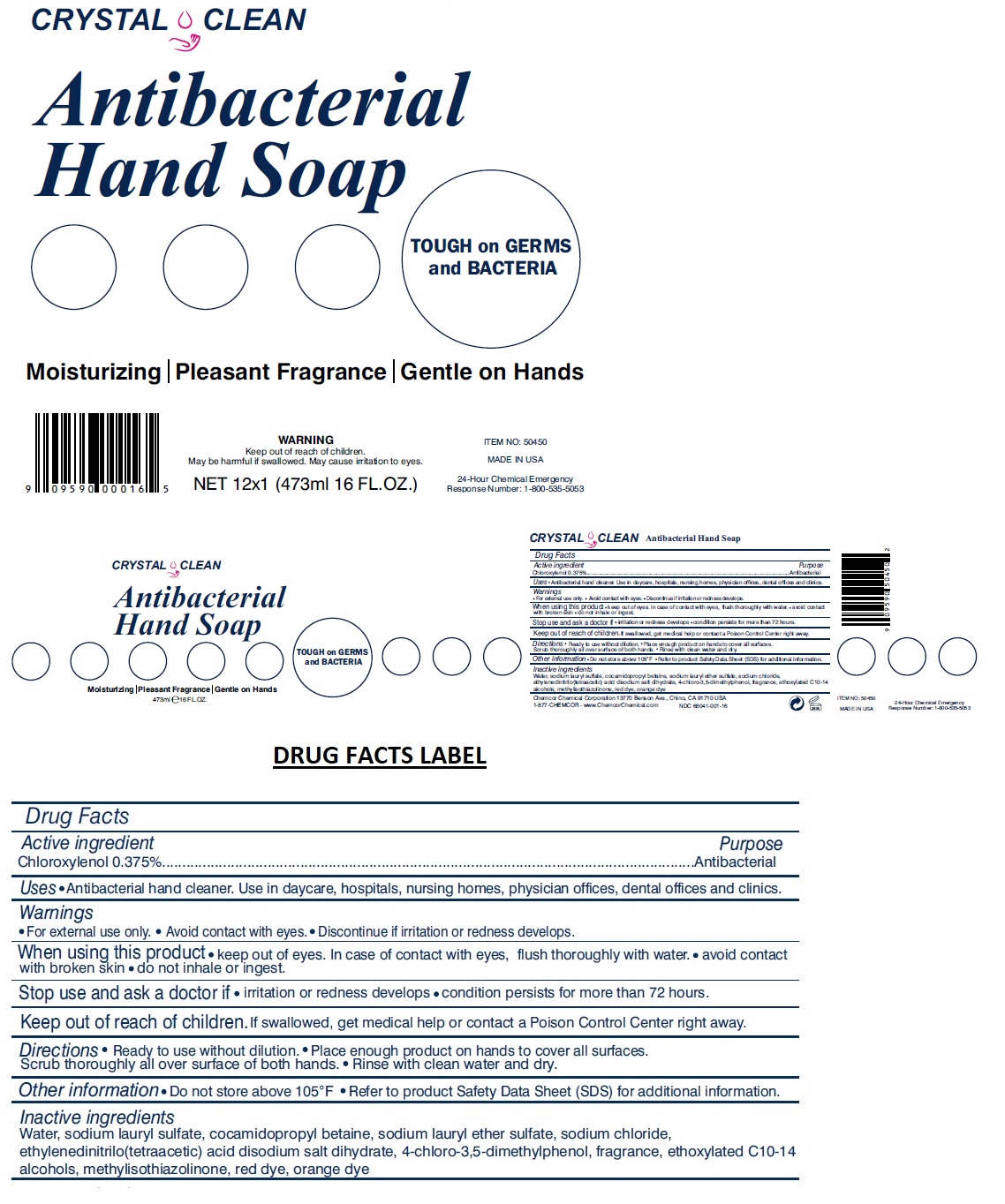 DRUG LABEL: Crystal Clean Antibacterial HandSoap
NDC: 68041-001 | Form: LIQUID
Manufacturer: Chemcor Chemical Corporation
Category: otc | Type: HUMAN OTC DRUG LABEL
Date: 20230102

ACTIVE INGREDIENTS: CHLOROXYLENOL 0.00375 mg/1 mL
INACTIVE INGREDIENTS: WATER; SODIUM LAURYL SULFATE; COCAMIDOPROPYL BETAINE; SODIUM LAURETH-3 SULFATE; SODIUM CHLORIDE; EDETATE DISODIUM; C10-16 ALKETH-1; METHYLISOTHIAZOLINONE; FD&C RED NO. 40; ACID ORANGE 20

CRYSTAL CLEAN Antibacterial Hand Soap

Active ingredient

Chloroxylenol 0.375%

Purpose

Antibacterial

INDICATIONS AND USAGE

Uses • Antibacterial hand cleaner. Use in daycare, hospitals, nursing homes, physician offices, dental offices and clinics.

Warnings

•For external use only. • Avoid contact with eyes. • Discontinue if irritation or redness develops.

When using this product • keep out of eyes. In case of contact with eyes, flush thoroughly with water. • avoid contact with broken skin • do not inhale or ingest.

Stop use and ask a doctor if • irritation or redness develops • condition persists for more than 72 hours.

Keep out of reach of children. If swallowed, get medical help or contact a Poison Control Center right away

DOSAGE AND ADMINISTRATION

Directions • Ready to use without dilution. • Place enough product on hands to cover all surfaces. Scrub thoroughly all over surface of both hands. • Rinse with clean water and dry.

Other information • Do not store above 105°F • Refer to product Safety Data Sheet (SDS) for additional information.

Inactive ingredients

Water, sodium lauryl sulfate, cocamidopropyl betaine, sodium lauryl ether sulfate, sodium chloride, ethylenedinitrilo(tetraacetic) acid disodium salt dihydrate, 4-chloro-3,5-dimethylphenol, fragrance, ethoxylated C10-14 alcohols, methylisothiazolinone, red dye, orange dye

TOUGH on GERMS and BACTERIA

Moisturizing | Pleasant Fragrance | Gentle on Hands

May be harmful if swallowed. May cause irritation to eyes.

Chemcor Chemical Corporation 13770 Benson Ave., Chino, CA 91710 USA

1-877-CHEMCOR - www.ChemcorChemical.com

MADE IN USA

24-Hour Chemical Emergency

Response Number: 1-800-535-5053